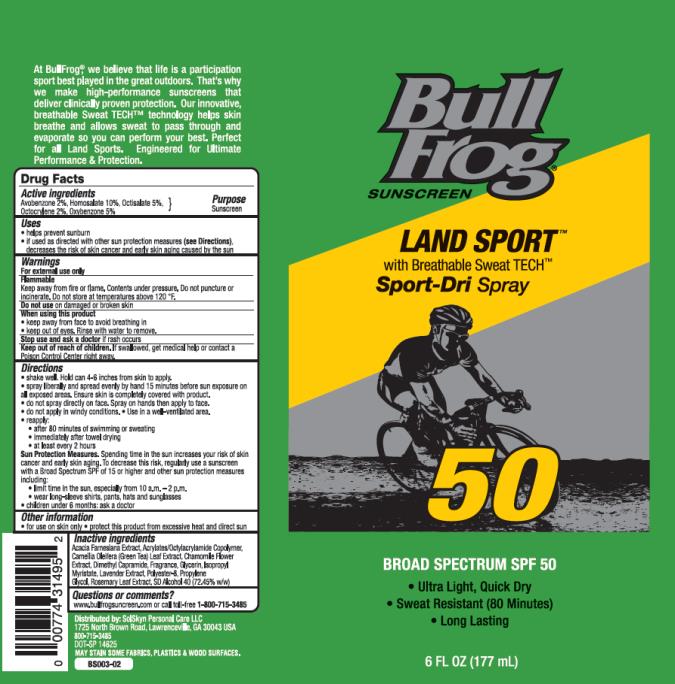 DRUG LABEL: BullFrog SPF50 Land Sport C-Spray
NDC: 70281-333 | Form: SPRAY
Manufacturer: SolSkyn Personal Care LLC
Category: otc | Type: HUMAN OTC DRUG LABEL
Date: 20170807

ACTIVE INGREDIENTS: AVOBENZONE 2 g/100 g; HOMOSALATE 10 g/100 g; OCTISALATE 5 g/100 g; OCTOCRYLENE 2 g/100 g; OXYBENZONE 5 g/100 g
INACTIVE INGREDIENTS: VACHELLIA FARNESIANA FLOWER; .ALPHA.-TOCOPHEROL ACETATE, D-; CAMELLIA OLEIFERA LEAF; CHAMAEMELUM NOBILE FLOWER; DIMETHYL CAPRAMIDE; GLYCERIN; ISOPROPYL MYRISTATE; LAVANDULA ANGUSTIFOLIA FLOWER; POLYESTER-8 (1400 MW, CYANODIPHENYLPROPENOYL CAPPED); PROPYLENE GLYCOL; ROSEMARY; ALCOHOL

BullFrog LandSport SPF50 CS 177ml

Product

BullFrog SPF50 Land Sport C-Spray

Active Ingredients

Avobenzone 2%, Homosalate 10%, Octisalate 5%, Octocrylene 2%, Oxybenzone 5%

Purpose

Sunscreen

Uses

- helps prevent sunburn
- if used as directed with other sun protection measures (see Directions), decreases the risk of skin cancer and early skin aging caused by the sun

Warnings

- For external use only
- Flammable: keep away from fire or flame. Contents under pressure. Do not puncture or incinerate. Do not store at temperatures above 120°F.

Do not use

- on damaged or broken skin.

When using this product:

- keep away from face to avoid breathing in
- keep out of eyes. Rinse with water to remove.

Keep out of reach of children.

- If swallowed, get medical help or contact a Poison Control Center right away.

Directions

- shake well. Hold can 4-6 inches from skin to apply.
- spray liberally and spread evenly by hand 15 minutes before sun exposure on all exposed areas. Ensure skin is completely covered with product.
- do not spray directly on face. Spray on hands then apply to face.
- do not apply in windy conditions.
- use in a well-ventilated area.
- re-apply:
  • after 80 minutes of swimming or sweating
  • immediately after towel drying
  • at least every 2 hours
- Sun Protection Measures. Spending time in the sun increases your risk of skin cancer and early skin aging. To decrease this risk, regularly use a sunscreen with a broad spectrum SPF of 15 or higher and other sun protection measures including:
- limit time in the sun, especially from 10 a.m.-2 p.m.
- wear long-sleeved shirts, pants, hats and sunglasses
- children under 6 months: ask a doctor

Other information

- for use on skin only
- protect this product from excessive heat and direct sun

Inactive Ingredients

Acacia Farnesiana Extract, Acrylates/Octylacrylamide Copolymer, Camellia Oleifera (Green Tea) Leaf Extract, Chamomile Flower Extract, Dimethyl Capramide, Fragrance, Glycerin, Isopropyl Myristate, Lavender Extract, Polyester-8, Propylene Glycol, Rosemary Leaf Extract, SD Alcohol 40 (71.45% w/w)

Questions or comments?

www.bullfrogsunscreen.com or call toll-free 1-800-715-3485

MAY STAIN SOME FABRICS, PLASTICS AND WOOD SURFACES.

PRINCIPAL DISPLAY PANEL

Bull Frog
Sunscreen
Landsport
SPF 50